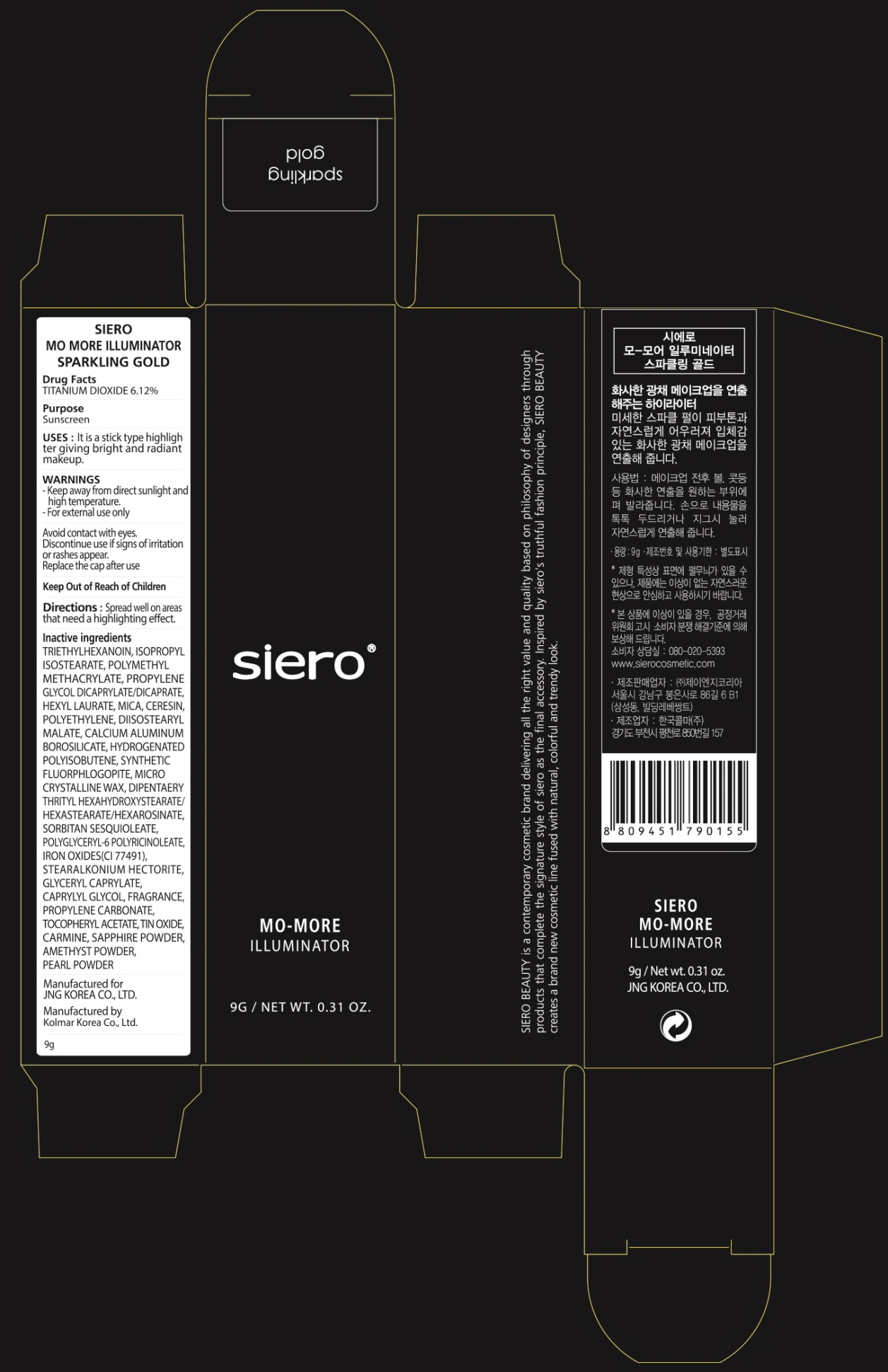 DRUG LABEL: SIERO MO MORE ILLUMINATOR SPARKLING GOLD
NDC: 71472-210 | Form: STICK
Manufacturer: JNG KOREA CO.,LTD.
Category: otc | Type: HUMAN OTC DRUG LABEL
Date: 20170630

ACTIVE INGREDIENTS: TITANIUM DIOXIDE 0.55 g/9 g
INACTIVE INGREDIENTS: TRIETHYLHEXANOIN; ISOPROPYL ISOSTEARATE

ACTIVE INGREDIENT

Active ingredients: TITANIUM DIOXIDE 6.12%

INACTIVE INGREDIENT

Inactive ingredients: TRIETHYLHEXANOIN, ISOPROPYL ISOSTEARATE, POLYMETHYL METHACRYLATE, PROPYLENE GLYCOL DICAPRYLATE/DICAPRATE, HEXYL LAURATE, MICA, CERESIN, POLYETHYLENE, DIISOSTEARYL MALATE, CALCIUM ALUMINUM BOROSILICATE, HYDROGENATED POLYISOBUTENE, SYNTHETIC FLUORPHLOGOPITE, MICROCRYSTALLINE WAX, DIPENTAERYTHRITYL HEXAHYDROXYSTEARATE/HEXASTEARATE/HEXAROSINATE, SORBITAN SESQUIOLEATE, POLYGLYCERYL-6 POLYRICINOLEATE, IRON OXIDES(CI 77491), STEARALKONIUM HECTORITE, GLYCERYL CAPRYLATE, CAPRYLYL GLYCOL, FRAGRANCE, PROPYLENE CARBONATE, TOCOPHERYL ACETATE, TIN OXIDE, CARMINE, SAPPHIRE POWDER, AMETHYST POWDER, PEARL POWDER

PURPOSE

Purpose: Sunscreen

WARNINGS

Warnings: - Keep away from direct sunlight and high temperature. - For external use only Avoid contact with eyes. Discontinue use if signs of irritation or rashes appear. Replace the cap after use. Keep Out of Reach of Children

DESCRIPTION

Uses: It is a stick type highlighter giving bright and radiant makeup.

Directions: Spread well on areas that need a highlighting effect.